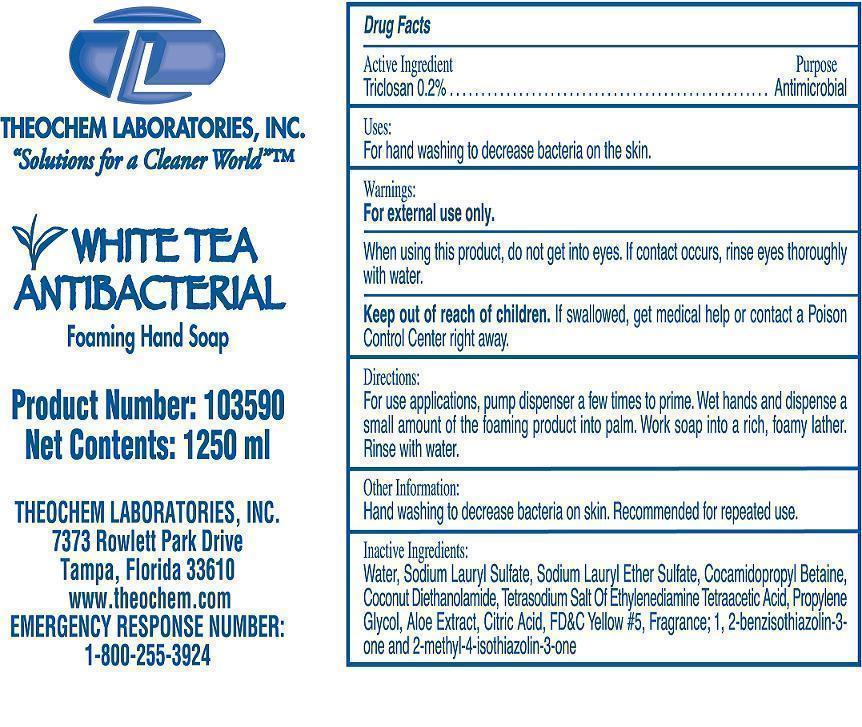 DRUG LABEL: White Tea Antibacterial
NDC: 68878-131 | Form: SOAP
Manufacturer: Theochem Laboratories, Inc
Category: otc | Type: HUMAN OTC DRUG LABEL
Date: 20131212

ACTIVE INGREDIENTS: TRICLOSAN .002 g/1 mL
INACTIVE INGREDIENTS: WATER

White Tea Antibacterial
Foaming Hand Soap

Active Ingredient

Triclosan 0.2%

Purpose

Antimicrobial

Uses

For hand washing to decrease bacteria on the skin.

Warnings:

For external use only.
When using this product, do not get into eyes. If contact occurs, rinse eyes thoroughly with water.

Keep out of reach of children.

If swallowed, get medical help or contact a Poison Control Center right away.

Directions:

For use applications, pump dispenser a few times to prime. Wet hands and dispense a small amount of the foamimg product into palm.
Work soap into a rich, foamy lather. Rinse with water.

Other Information:

Hand washing to decrease bacteria on skin. Recommended for repeated use.

Inactive Ingredients:

Water, Sodium Lauryl Sulfate, Sodium Lauryl Ether Sulfate, Cocamidopropyl Betaine, Coconut Diethanolamide, Tetrasodium Salt of Ehylenediamine Tetraacetic Acid, Propylene Glycol, Aloe Extract, Citric Acid, FD&C Yellow # 5, Fragrance; 1, 2-benzisothiazolin-3-one and 2-methyl-4-isothiazolin-3-one